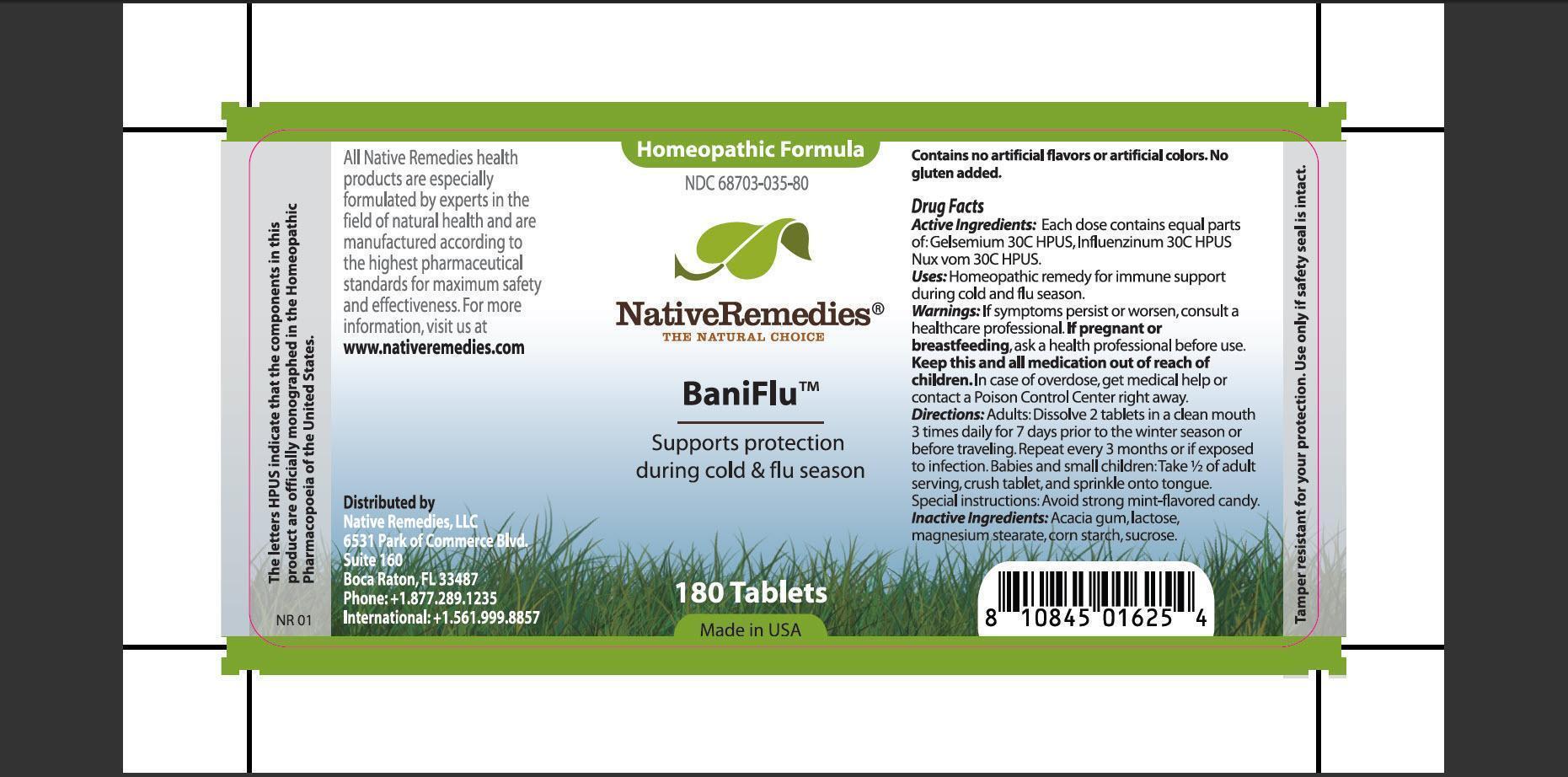 DRUG LABEL: BaniFlu
                
NDC: 68703-035 | Form: TABLET
Manufacturer: Native Remedies, LLC
Category: homeopathic | Type: HUMAN OTC DRUG LABEL
Date: 20130102

ACTIVE INGREDIENTS: GELSEMIUM SEMPERVIRENS ROOT 30 [hp_C]/1 1; INFLUENZA A VIRUS A/NEW CALEDONIA/20/99 (H1N1) ANTIGEN (PROPIOLACTONE INACTIVATED) 30 [hp_C]/1 1; INFLUENZA A VIRUS A/PANAMA/2007/99 (H3N2) ANTIGEN (PROPIOLACTONE INACTIVATED) 30 [hp_C]/1 1; INFLUENZA B VIRUS B/HONG KONG/330/2001 ANTIGEN (PROPIOLACTONE INACTIVATED) 30 [hp_C]/1 1; STRYCHNOS NUX-VOMICA SEED 30 [hp_C]/1 1
INACTIVE INGREDIENTS: ACACIA; LACTOSE; MAGNESIUM STEARATE; STARCH, CORN; SUCROSE

BaniFlu

PURPOSE

Supports protection during cold and flu season

ACTIVE INGREDIENT

Active Ingredients: Each dose contains equal parts of: Gelsemium 30C HPUS, Influenzinum 30C HPUS, Nux vom 30C HPUS.

INDICATIONS AND USAGE

Uses: Homeopathic remedy for immune support during cold and flu season.

WARNINGS

Warnings: If symptoms persist or worsen, consult a healthcare professional.

PREGNANCY OR BREAST FEEDING

If pregnant or breastfeeding, ask a health professional before use.

KEEP OUT OF REACH OF CHILDREN

Keep this and all medication out of reach of children.

OVERDOSAGE

In case of overdose, get medical help or contact a Poison Control Center right away.

DOSAGE AND ADMINISTRATION

Directions: Adults: Dissolve 2 tablets in a clean mouth 3 times daily for 7 days prior to the winter season or before traveling. Repeat every 3 months or if exposed to infection. Babies and small children: Take 1/4 of adult serving, crush tablet, and sprinkle onto tongue.

Special instructions: Avoid strong mint-flavored candy.

INACTIVE INGREDIENT

Inactive Ingredients: Acacia gum, lactose, magnesium stearate, corn starch, sucrose.

PATIENT COUNSELING INFORMATION

The letters HPUS indicate that the components in this product are officially monographed in the Homeopathic Pharmacopoeia of the United States.

All Native Remedies health products are especially formulated by experts in the field of natural health and are manufactured according to the highest pharmaceutical standards for maximum safety and effectiveness. For more information, visit us at www.nativeremedies.com

Distributed by
Native Remedies, LLC
6531 Park of Commerce Blvd.
Suite 160
Boca Raton, FL 33487
Phone: +1.877.289.1235
International: +1.561.999.8857

Contains no artificial flavors or artificial colors. No gluten added.

STORAGE AND HANDLING

Tamper resistant seal for your protection. Use only if safety seal is intact.